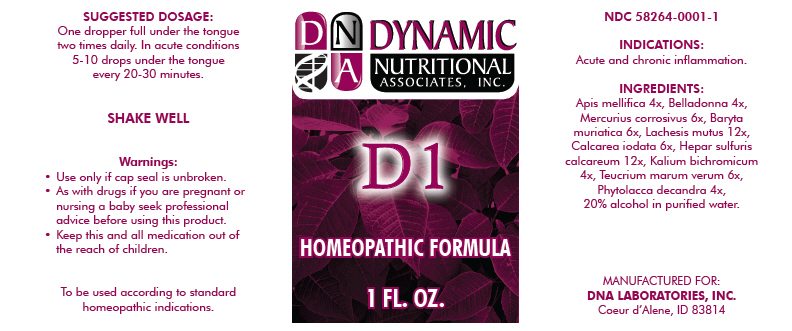 DRUG LABEL: D1
NDC: 58264-0001 | Form: SOLUTION
Manufacturer: DNA Labs, Inc.
Category: homeopathic | Type: HUMAN OTC DRUG LABEL
Date: 20180129

ACTIVE INGREDIENTS: APIS MELLIFERA 4 [hp_X]/1 mL; BELLADONNA LEAF 4 [hp_X]/1 mL; MERCURIC CHLORIDE 6 [hp_X]/1 mL; BARIUM CHLORIDE DIHYDRATE 6 [hp_X]/1 mL; LACHESIS MUTA VENOM 12 [hp_X]/1 mL; CALCIUM IODIDE 6 [hp_X]/1 mL; CALCIUM SULFIDE 12 [hp_X]/1 mL; POTASSIUM DICHROMATE 4 [hp_X]/1 mL; TEUCRIUM MARUM 6 [hp_X]/1 mL; PHYTOLACCA AMERICANA WHOLE 4 [hp_X]/1 mL
INACTIVE INGREDIENTS: Alcohol; Water

D1

NDC 58264-0001-1

INDICATIONS AND USAGE

INDICATIONS

Acute and chronic inflammation.

ACTIVE INGREDIENT

INGREDIENTS

Apis mellifica 4x, Belladonna 4x, Mercurius corrosivus 6x, Baryta muriatica 6x, Lachesis mutus 12x, Calcarea iodata 6x, Hepar sulfuris calcareum 12x, Kalium bichromicum 4x, Teucrium marum verum 6x, Phytolacca decandra 4x, 20% alcohol in purified water.

SUGGESTED DOSAGE

One dropper full under the tongue two times daily. In acute conditions 5-10 drops under the tongue every 20-30 minutes.

STORAGE AND HANDLING

SHAKE WELL

Warnings

- Use only if cap seal is unbroken.

PREGNANCY OR BREAST FEEDING

- As with drugs if you are pregnant or nursing a baby seek professional advice before using this product.

KEEP OUT OF REACH OF CHILDREN

- Keep this and all medication out of the reach of children.

To be used according to standard homeopathic indications.

PRINCIPAL DISPLAY PANEL - 1 FL. OZ. Bottle Label

DYNAMIC
NUTRITIONAL
ASSOCIATES, INC.

D 1

HOMEOPATHIC FORMULA

1 FL. OZ.